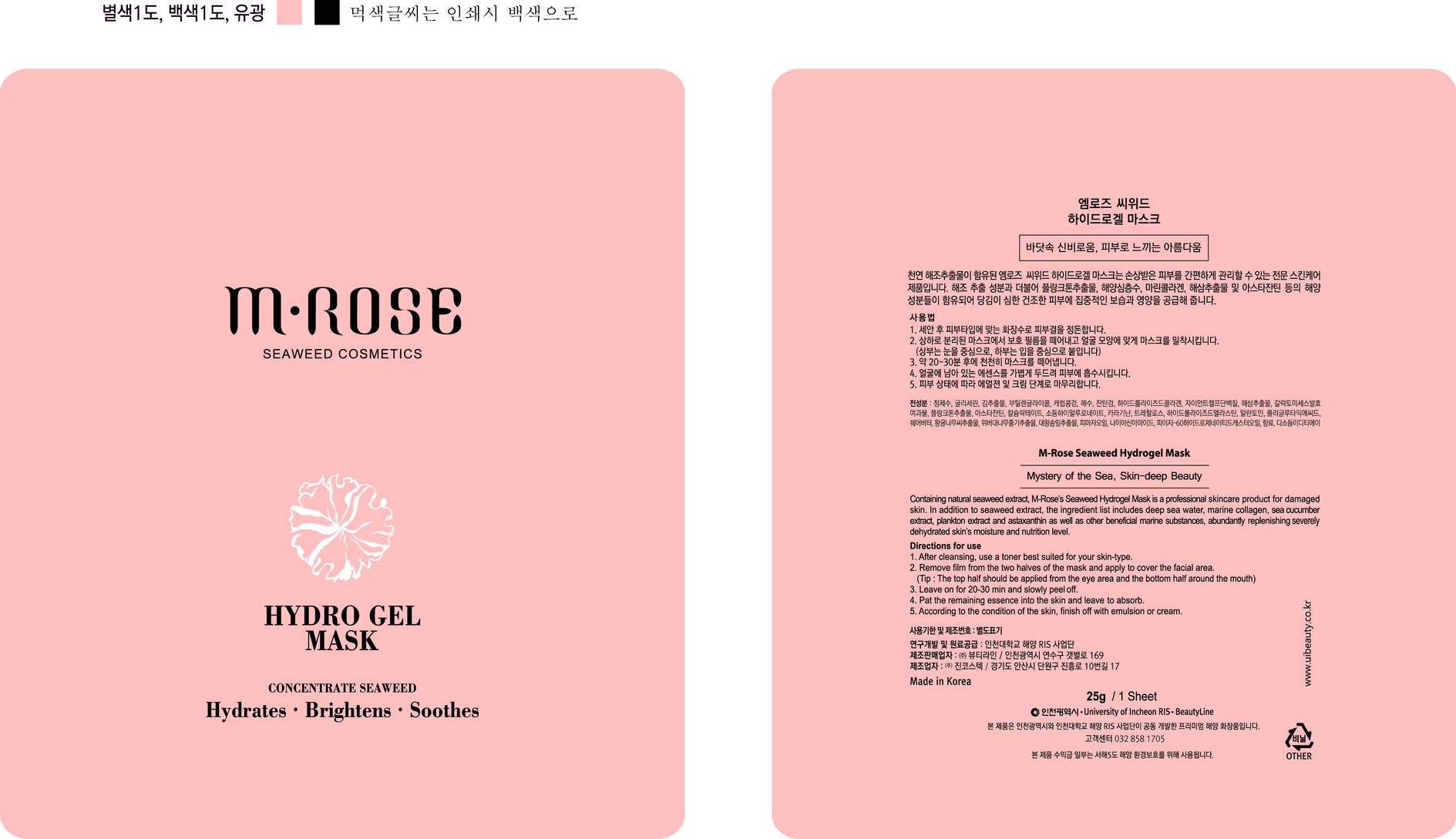 DRUG LABEL: M-Rose Seaweed Hydrogel Mask
NDC: 69327-9001 | Form: PATCH
Manufacturer: Beauty Line Co., Ltd.
Category: otc | Type: HUMAN OTC DRUG LABEL
Date: 20141025

ACTIVE INGREDIENTS: ALLANTOIN 0.2 g/100 g
INACTIVE INGREDIENTS: WATER; BUTYLENE GLYCOL; HYALURONATE SODIUM

Drug Facts

ACTIVE INGREDIENT

allantoin

INACTIVE INGREDIENT

water, butylene glycol, sea water, xanthan gum, hydrolyzed collagen, calcium lactate, polyglutamic acid, etc

PURPOSE

skin protectant

keep out or reach of the children

INDICATIONS AND USAGE

1. First, cleanse your face and apply serum and emulsion. Then place the mask pack over the entire forehead nose to a thickness of about 1 mm.
2. Smooth along the jaw line.
3. Place over the cheeks and around the mouth. When the mask has completely dried (approximately 15-20 minutes), gently peel off from the chin.
4. Press the face with both palms from the center toward the outer edge of the face, pressing the skin lightly.
5. With fingertips, press on the areas around the eyes and the mouth, starting from the center of the face and moving outward.

WARNINGS

-If in contact with the eyes, wash out thoroughty with water If the symptoms are servere, seek medical advice immediately
-This product is for exeternal use only. Do not use for internal use
-If possible, avoid direct sunlight and store in cool and area of low humidity
-In order to maintain the quality of the product and avoid misuse
-Avoid placing the product near fire and store out in reach of children

DOSAGE AND ADMINISTRATION

for external use only